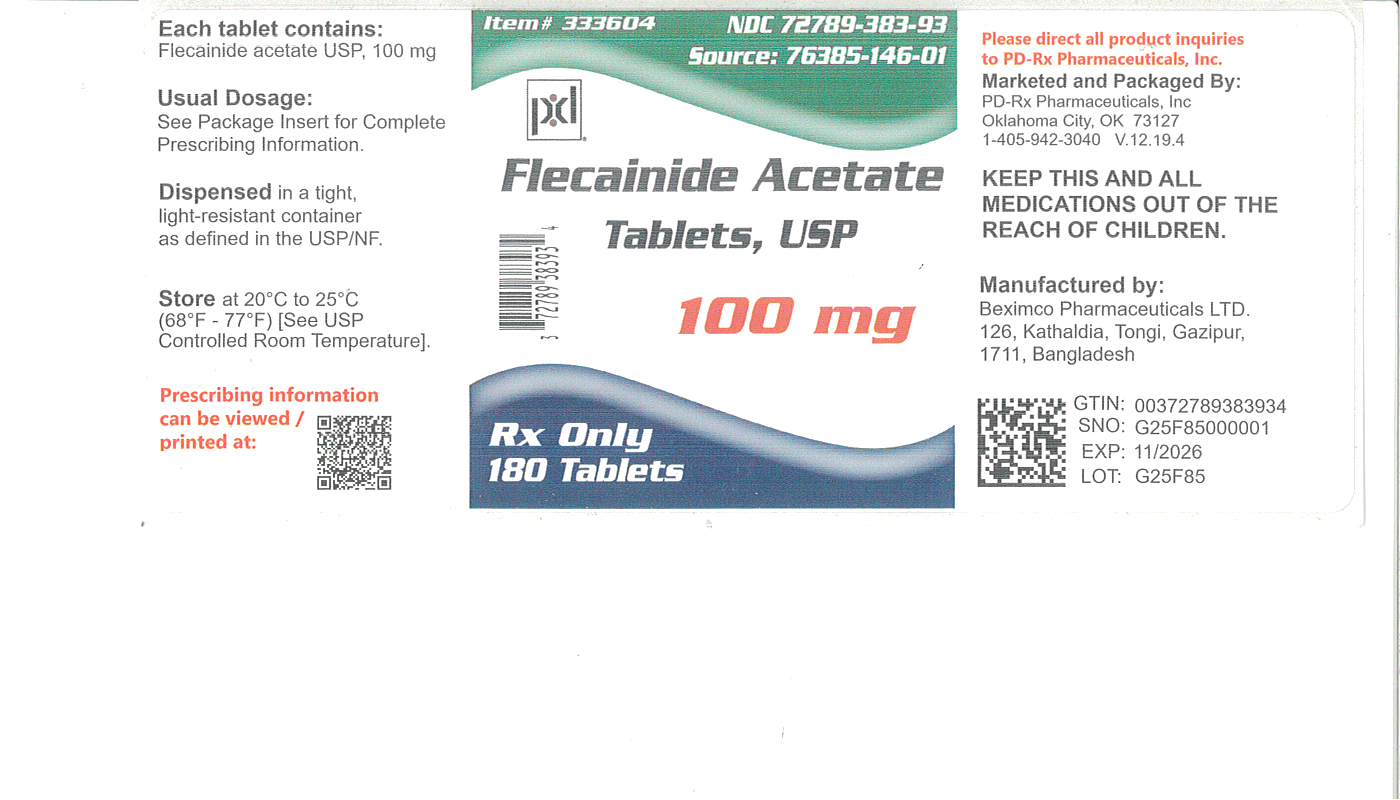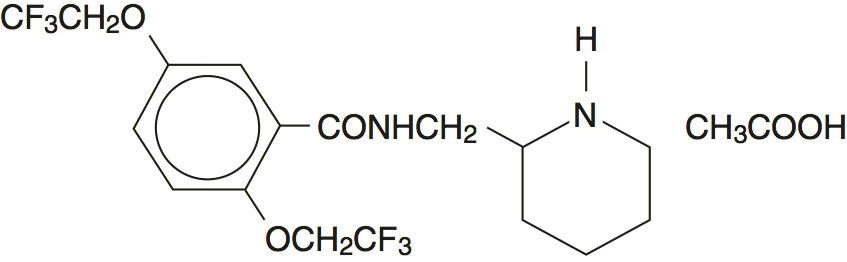 DRUG LABEL: Flecainide Acetate
NDC: 72789-383 | Form: TABLET
Manufacturer: PD-Rx Pharmaceuticals, Inc.
Category: prescription | Type: HUMAN PRESCRIPTION DRUG LABEL
Date: 20260226

ACTIVE INGREDIENTS: FLECAINIDE ACETATE 100 mg/1 1
INACTIVE INGREDIENTS: MAGNESIUM STEARATE; CELLULOSE, MICROCRYSTALLINE; CROSCARMELLOSE SODIUM; STARCH, PREGELATINIZED CORN

Flecainide Acetate Tablets USP

DESCRIPTION

Flecainide acetate tablets, USP are an antiarrhythmic drug available in tablets of 50, 100, or 150 mg for oral administration. Flecainide acetate is benzamide, N-(2-piperidinylmethyl)-2,5-bis(2,2,2-trifluoroethoxy)-monoacetate. The structural formula is given below.

Flecainide acetate is a white crystalline substance with a pKaof 9.3. It has an aqueous solubility of 48.4 mg/mL at 37°C.

Flecainide acetate tablets, USP also contain: croscarmellose sodium, hydrogenated vegetable oil, magnesium stearate, microcrystalline cellulose, and pregelatinized starch.

CLINICAL PHARMACOLOGY

Flecainide acetate tablets, USP have local anesthetic activity and belong to the membrane stabilizing (Class 1) group of antiarrhythmic agents; they have electrophysiologic effects characteristic of the IC class of antiarrhythmics.

Electrophysiology

In man, flecainide acetate tablets, USP produce a dose-related decrease in intracardiac conduction in all parts of the heart with the greatest effect on the His-Purkinje system (H-V conduction). Effects upon atrioventricular (AV) nodal conduction time and intra-atrial conduction times, although present, are less pronounced than those on ventricular conduction velocity. Significant effects on refractory periods were observed only in the ventricle. Sinus node recovery times (corrected) following pacing and spontaneous cycle lengths are somewhat increased. This latter effect may become significant in patients with sinus node dysfunction. (See WARNINGS.)

Flecainide acetate tablets, USP cause a dose-related and plasma-level related decrease in single and multiple PVCs and can suppress recurrence of ventricular tachycardia. In limited studies of patients with a history of ventricular tachycardia, flecainide acetate tablets, USP have been successful 30 to 40% of the time in fully suppressing the inducibility of arrhythmias by programmed electrical stimulation. Based on PVC suppression, it appears that plasma levels of 0.2 to 1 mcg/mL may be needed to obtain the maximal therapeutic effect. It is more difficult to assess the dose needed to suppress serious arrhythmias, but trough plasma levels in patients successfully treated for recurrent ventricular tachycardia were between 0.2 and 1 mcg/mL. Plasma levels above 0.7 to 1 mcg/mL are associated with a higher rate of cardiac adverse experiences such as conduction defects or bradycardia. The relation of plasma levels to proarrhythmic events is not established, but dose reduction in clinical trials of patients with ventricular tachycardia appears to have led to a reduced frequency and severity of such events.

Hemodynamics

Flecainide does not usually alter heart rate, although bradycardia and tachycardia have been reported occasionally.
In animals and isolated myocardium, a negative inotropic effect of flecainide has been demonstrated. Decreases in ejection fraction, consistent with a negative inotropic effect, have been observed after single administration of 200 to 250 mg of the drug in man; both increases and decreases in ejection fraction have been encountered during multidose therapy in patients at usual therapeutic doses. (See WARNINGS.)

Metabolism in Humans

Following oral administration, the absorption of flecainide is nearly complete. Peak plasma levels are attained at about three hours in most individuals (range, 1 to 6 hours). Flecainide does not undergo any consequential presystemic biotransformation (first-pass effect). Food or antacid do not affect absorption. Milk, however, may inhibit absorption in infants. A reduction in flecainide dosage should be considered when milk is removed from the diet of infants.

The apparent plasma half-life averages about 20 hours and is quite variable (range, 12 to 27 hours) after multiple oral doses in patients with premature ventricular contractions (PVCs). With multiple dosing, plasma levels increase because of its long half-life with steady-state levels approached in 3 to 5 days; once at steady-state, no additional (or unexpected) accumulation of drug in plasma occurs during chronic therapy. Over the usual therapeutic range, data suggest that plasma levels in an individual are approximately proportional to dose, deviating upwards from linearity only slightly (about 10 to 15% per 100 mg on average).

In healthy subjects, about 30% of a single oral dose (range, 10 to 50%) is excreted in urine as unchanged drug. The two major urinary metabolites are meta-O-dealkylated flecainide (active, but about one-fifth as potent) and the meta-O-dealkylated lactam of flecainide (non-active metabolite). These two metabolites (primarily conjugated) account for most of the remaining portion of the dose. Several minor metabolites (3% of the dose or less) are also found in urine; only 5% of an oral dose is excreted in feces. In patients, free (unconjugated) plasma levels of the two major metabolites are very low (less than 0.05 mcg/mL).

In vitrometabolic studies have confirmed that cytochrome P450IID6 is involved in the metabolism in flecainide.

When urinary pH is very alkaline (8 or higher), as may occur in rare conditions (e.g., renal tubular acidosis, strict vegetarian diet), flecainide elimination from plasma is much slower.

The elimination of flecainide from the body depends on renal function (i.e., 10 to 50% appears in urine as unchanged drug). With increasing renal impairment, the extent of unchanged drug excretion in urine is reduced and the plasma half-life of flecainide is prolonged. Since flecainide is also extensively metabolized, there is no simple relationship between creatinine clearance and the rate of flecainide elimination from plasma. (See DOSAGE AND ADMINISTRATION.)

In patients with NYHA class III congestive heart failure (CHF), the rate of flecainide elimination from plasma (mean half-life, 19 hours) is moderately slower than for healthy subjects (mean half-life, 14 hours), but similar to the rate for patients with PVCs without CHF. The extent of excretion of unchanged drug in urine is also similar. (See DOSAGE AND ADMINISTRATION.)

Under one year of age, currently available data are limited but suggest that the half-life at birth may be as long as 29 hours, decreasing to 11 to 12 hours by three months of age and 6 hours by one year of age. The pharmacokinetics in hydropic infants have not been studied, but case reports suggest prolonged elimination. In children aged 1 year to 12 years the half-life is approximately 8 hours. In adolescents (age 12 to 15) the plasma elimination half-life is approximately 11 to 12 hours. Since milk may inhibit absorption in infants, a reduction in flecainide dosage should be considered when milk is removed from the diet (e.g., gastroenteritis, weaning). Plasma trough flecainide levels should be monitored during major changes in dietary milk intake.

From age 20 to 80, plasma levels are only slightly higher with advancing age; flecainide elimination from plasma is somewhat slower in elderly subjects than in younger subjects. Patients up to age 80+ have been safely treated with usual dosages.

The extent of flecainide binding to human plasma proteins is about 40% and is independent of plasma drug level over the range of 0.015 to about 3.4 mcg/mL. Thus, clinically significant drug interactions based on protein binding effects would not be expected.

Hemodialysis removes only about 1% of an oral dose as unchanged flecainide.

Small increases in plasma digoxin levels are seen during coadministration of flecainide with digoxin. Small increases in both flecainide and propranolol plasma levels are seen during coadministration of these two drugs. (See PRECAUTIONS: Drug Interactions.)

Clinical Trials

In two randomized, crossover, placebo-controlled clinical trials of 16 weeks double-blind duration, 79% of patients with paroxysmal supraventricular tachycardia (PSVT) receiving flecainide were attack free, whereas 15% of patients receiving placebo remained attack free. The median time-before-recurrence of PSVT in patients receiving placebo was 11 to 12 days, whereas over 85% of patients receiving flecainide had no recurrence at 60 days.

n two randomized, crossover, placebo-controlled clinical trials of 16 weeks double-blind duration, 31% of patients with paroxysmal atrial fibrillation/flutter (PAF) receiving flecainide were attack free, whereas 8% receiving placebo remained attack free. The median time-before-recurrence of PAF in patients receiving placebo was about 2 to 3 days, whereas for those receiving flecainide the median time-before-recurrence was 15 days.

INDICATIONS AND USAGE

In patients without structural heart disease, flecainide acetate tablets, USP are indicated for the prevention of:

•paroxysmal supraventricular tachycardias (PSVT), including atrioventricular nodal reentrant tachycardia, atrioventricular reentrant tachycardia and other supraventricular tachycardias of unspecified mechanism associated with disabling symptoms

•paroxysmal atrial fibrillation/flutter (PAF) associated with disabling symptoms Flecainide acetate tablets, USP are also indicated for the prevention of:

•Documented ventricular arrhythmias, such as sustained ventricular tachycardia (sustained VT), that in the judgment of the physician are life-threatening.

Use of flecainide acetate tablets, USP for the treatment of sustained VT, like other antiarrhythmics, should be initiated in the hospital. The use of flecainide acetate is not recommended in patients with less severe ventricular arrhythmias even if the patients are symptomatic.

Because of the proarrhythmic effects of flecainide acetate tablets, USP, their use should be reserved for patients in whom, in the opinion of the physician, the benefits of treatment outweigh the risks.

Flecainide acetate tablets, USP should not be used in patients with recent myocardial infarction. (See BOXED WARNINGS.)

Use of flecainide acetate tablets, USP in chronic atrial fibrillation has not been adequately studied and is not recommended. (See BOXED WARNINGS.)

As is the case for other antiarrhythmic agents, there is no evidence from controlled trials that the use of flecainide acetate tablets, USP favorably affect survival or the incidence of sudden death.

CONTRAINDICATIONS

Flecainide acetate tablets, USP are contraindicated in patients with pre-existing second- or third-degree AV block, or with right bundle branch block when associated with a left hemiblock (bifascicular block), unless a pacemaker is present to sustain the cardiac rhythm should complete heart block occur. Flecainide acetate tablets, USP are also contraindicated in the presence of cardiogenic shock or known hypersensitivity to the drug.

WARNINGS

BOXED WARNING

Mortality

Flecainide acetate was included in the National Heart Lung and Blood Institute’s Cardiac Arrhythmia Suppression Trial (CAST), a long-term, multicenter, randomized, double-blind study in patients with asymptomatic non-life-threatening ventricular arrhythmias who had a myocardial infarction more than six days but less than two years previously. An excessive mortality or non-fatal cardiac arrest rate was seen in patients treated with flecainide acetate compared with that seen in patients assigned to a carefully matched placebo-treated group. This rate was 16/315 (5.1%) for flecainide acetate and 7/309 (2.3%) for the matched placebo. The average duration of treatment with flecainide acetate in this study was ten months.

The applicability of the CAST results to other populations (e.g., those without recent myocardial infarction) is uncertain, but at present, it is prudent to consider the risks of Class IC agents (including flecainide acetate), coupled with the lack of any evidence of improved survival, generally unacceptable in patients without life-threatening ventricular arrhythmias, even if the patients are experiencing unpleasant, but not life-threatening, symptoms or signs.

Ventricular Pro-arrhythmic Effects in Patients with Atrial Fibrillation/Flutter

A review of the world literature revealed reports of 568 patients treated with oral flecainide acetate for paroxysmal atrial fibrillation/flutter (PAF). Ventricular tachycardia was experienced in 0.4% (2/568) of these patients. Of 19 patients in the literature with chronic atrial fibrillation (CAF), 10.5% (2) experienced VT or VF. FLECAINIDE IS NOT RECOMMENDED FOR USE IN PATIENTS WITH CHRONIC ATRIAL FIBRILLATION. Case reports of ventricular proarrhythmic effects in patients treated with flecainide for atrial fibrillation/flutter have included increased PVCs, VT, ventricular fibrillation (VF), and death.

As with other Class I agents, patients treated with flecainide acetate for atrial flutter have been reported with 1:1 atrioventricular conduction due to slowing the atrial rate. A paradoxical increase in the ventricular rate also may occur in patients with atrial fibrillation who receive flecainide acetate. Concomitant negative chronotropic therapy such as digoxin or beta-blockers may lower the risk of this complication.

PROARRHYTHMIC EFFECTS

Flecainide acetate, like other antiarrhythmic agents, can cause new or worsened supraventricular or ventricular arrhythmias. Ventricular proarrhythmic effects range from an increase in frequency of PVCs to the development of more severe ventricular tachycardia, e.g., tachycardia that is more sustained or more resistant to conversion to sinus rhythm, with potentially fatal consequences. In studies of ventricular arrhythmia patients treated with flecainide acetate, three-fourths of proarrhythmic events were new or worsened ventricular tachyarrhythmias, the remainder being increased frequency of PVCs or new supraventricular arrhythmias. In patients treated with flecainide for sustained ventricular tachycardia, 80% (51/64) of proarrhythmic events occurred within 14 days of the onset of therapy. In studies of 225 patients with supraventricular arrhythmia (108 with paroxysmal supraventricular tachycardia and 117 with paroxysmal atrial fibrillation), there were 9 (4%) proarrhythmic events, 8 of them in patients with paroxysmal atrial fibrillation. Of the 9, 7 (including the one in a PSVT patient) were exacerbations of supraventricular arrhythmias (longer duration, more rapid rate, harder to reverse) while 2 were ventricular arrhythmias, including one fatal case of VT/VF and one wide complex VT (the patient showed inducible VT, however, after withdrawal of flecainide), both in patients with paroxysmal atrial fibrillation and known coronary artery disease.

It is uncertain if flecainide acetate’s risk of proarrhythmia is exaggerated in patients with chronic atrial fibrillation (CAF), high ventricular rate, and/or exercise. Wide complex tachycardia and ventricular fibrillation have been reported in two of 12 CAF patients undergoing maximal exercise tolerance testing.

In patients with complex ventricular arrhythmias, it is often difficult to distinguish a spontaneous variation in the patient’s underlying rhythm disorder from drug-induced worsening, so that the following occurrence rates must be considered approximations. Their frequency appears to be related to dose and to the underlying cardiac disease.

Among patients treated for sustained VT (who frequently also had CHF, a low ejection fraction, a history of myocardial infarction and/or an episode of cardiac arrest), the incidence of proarrhythmic events was 13% when dosage was initiated at 200 mg/day with slow upward titration, and did not exceed 300 mg/day in most patients. In early studies in patients with sustained VT utilizing a higher initial dose (400 mg/day) the incidence of proarrhythmic events was 26%; moreover, in about 10% of the patients treated proarrhythmic events resulted in death, despite prompt medical attention. With lower initial doses, the incidence of proarrhythmic events resulting in death decreased to 0.5% of these patients. Accordingly, it is extremely important to follow the recommended dosage schedule. (See DOSAGE AND ADMINISTRATION.)

The relatively high frequency of proarrhythmic events in patients with sustained VT and serious underlying heart disease, and the need for careful titration and monitoring, requires that therapy of patients with sustained VT be started in the hospital. (See DOSAGE AND ADMINISTRATION.)

HEART FAILURE

Flecainide acetate has a negative inotropic effect and may cause or worsen CHF, particularly in patients with cardiomyopathy, preexisting severe heart failure (NYHA functional class III or IV) or low ejection fractions (less than 30%). In patients with supraventricular arrhythmias new or worsened CHF developed in 0.4% (1/225) of patients. In patients with sustained ventricular tachycardia during a mean duration of 7.9 months of flecainide acetate therapy, 6.3% (20/317) developed new CHF. In patients with sustained ventricular tachycardia and a history of CHF, during a mean duration of 5.4 months of flecainide acetate therapy, 25.7% (78/304) developed worsened CHF. Exacerbation of preexisting CHF occurred more commonly in studies which included patients with class III or IV failure than in studies which excluded such patients. Flecainide acetate should be used cautiously in patients who are known to have a history of CHF or myocardial dysfunction. The initial dosage in such patients should be no more than 100 mg bid (see DOSAGE AND ADMINISTRATION) and patients should be monitored carefully. Close attention must be given to maintenance of cardiac function, including optimization of digitalis, diuretic, or other therapy. In cases where CHF has developed or worsened during treatment with flecainide acetate, the time of onset has ranged from a few hours to several months after starting therapy. Some patients who develop evidence of reduced myocardial function while on flecainide can continue on flecainide acetate with adjustment of digitalis or diuretics, others may require dosage reduction or discontinuation of flecainide acetate. When feasible, it is recommended that plasma flecainide levels be monitored. Attempts should be made to keep trough plasma levels below 0.7 to 1 mcg/mL.

Effects on Cardiac Conduction

Flecainide acetate slows cardiac conduction in most patients to produce dose-related increases in PR, QRS, and QT intervals. PR interval increases on average about 25% (0.04 seconds) and as much as 118% in some patients. Approximately one-third of patients may develop new first-degree AV heart block (PR interval ≥ 0.2 seconds). The QRS complex increases on average about 25% (0.02 seconds) and as much as 150% in some patients. Many patients develop QRS complexes with a duration of 0.12 seconds or more. In one study, 4% of patients developed new bundle branch block while on flecainide acetate. The degree of lengthening of PR and QRS intervals does not predict either efficacy or the development of cardiac adverse effects. In clinical trials, it was unusual for PR intervals to increase to 0.3 seconds or more, or for QRS intervals to increase to 0.18 seconds or more. Thus, caution should be used when such intervals occur, and dose reductions may be considered. The QT interval widens about 8%, but most of this widening (about 60% to 90%) is due to widening of the QRS duration. The JT interval (QT minus QRS) only widens about 4% on the average. Significant JT prolongation occurs in less than 2% of patients. There have been rare cases of Torsade de Pointes-type arrhythmia associated with flecainide acetate therapy.

Clinically significant conduction changes have been observed at these rates: sinus node dysfunction such as sinus pause, sinus arrest and symptomatic bradycardia (1.2%), second-degree AV block (0.5%) and third-degree AV block (0.4%). An attempt should be made to manage the patient on the lowest effective dose in an effort to minimize these effects. (See DOSAGE AND ADMINISTRATION.) If second- or third-degree AV block, or right bundle branch block associated with a left hemiblock occur, flecainide therapy should be discontinued unless a temporary or implanted ventricular pacemaker is in place to ensure an adequate ventricular rate.

Sick Sinus Syndrome (Bradycardia-Tachycardia Syndrome)

Flecainide acetate should be used only with extreme caution in patients with sick sinus syndrome because it may cause sinus bradycardia, sinus pause, or sinus arrest.

Effects on Pacemaker Thresholds

Flecainide acetate is known to increase endocardial pacing thresholds and may suppress ventricular escape rhythms. These effects are reversible if flecainide is discontinued. It should be used with caution in patients with permanent pacemakers or temporary pacing electrodes and should not be administered to patients with existing poor thresholds or nonprogrammable pacemakers unless suitable pacing rescue is available.

The pacing threshold in patients with pacemakers should be determined prior to instituting therapy with flecainide acetate, again after one week of administration and at regular intervals thereafter. Generally threshold changes are within the range of multiprogrammable pacemakers and, when these occur, a doubling of either voltage or pulse width is usually sufficient to regain capture.

Electrolyte Disturbances

Hypokalemia or hyperkalemia may alter the effects of Class I antiarrhythmic drugs. Preexisting hypokalemia or hyperkalemia should be corrected before administration of flecainide acetate.

Pediatric Use

The safety and efficacy of flecainide acetate in the fetus, infant, or child have not been established in double-blind, randomized, placebo-controlled trials. The proarrhythmic effects of flecainide acetate, as described previously, apply also to children. In pediatric patients with structural heart disease, flecainide acetate has been associated with cardiac arrest and sudden death. Flecainide acetate should be started in the hospital with rhythm monitoring. Any use of flecainide acetate in children should be directly supervised by a cardiologist skilled in the treatment of arrhythmias in children.

PRECAUTIONS

Drug Interactions

Flecainide has been administered to patients receiving digitalis preparations or beta-adrenergic blocking agents without adverse effects. During administration of multiple oral doses of flecainide to healthy subjects stabilized on a maintenance dose of digoxin, a 13% to 19% increase in plasma digoxin levels occurred at six hours postdose.

In a study involving healthy subjects receiving flecainide and propranolol concurrently, plasma flecainide levels were increased about 20% and propranolol levels were increased about 30% compared to control values. In this formal interaction study, flecainide and propranolol were each found to have negative inotropic effects; when the drugs were administered together, the effects were additive. The effects of concomitant administration of flecainide and propranolol on the PR interval were less than additive. In flecainide clinical trials, patients who were receiving beta blockers concurrently did not experience an increased incidence of side effects. Nevertheless, the possibility of additive negative inotropic effects of beta blockers and flecainide should be recognized.

Flecainide is not extensively bound to plasma proteins. In vitrostudies with several drugs which may be administered concomitantly showed that the extent of flecainide binding to human plasma proteins is either unchanged or only slightly less. Consequently, interactions with other drugs which are highly protein bound (e.g., anticoagulants) would not be expected. Flecainide has been used in a large number of patients receiving diuretics without apparent interaction. Limited data in patients receiving known enzyme inducers (phenytoin, phenobarbital, carbamazepine) indicate only a 30% increase in the rate of flecainide elimination. In healthy subjects receiving cimetidine (1 gm daily) for one week, plasma flecainide levels increased by about 30% and half-life increased by about 10%.

When amiodarone is added to flecainide therapy, plasma flecainide levels may increase two-fold or more in some patients, if flecainide dosage is not reduced. (See DOSAGE AND ADMINISTRATION.)

Drugs that inhibit cytochrome P450IID6, such as quinidine, might increase the plasma concentrations of flecainide in patients that are on chronic flecainide therapy; especially if these patients are extensive metabolizers.

There has been little experience with the coadministration of flecainide and either disopyramide or verapamil. Because both of these drugs have negative inotropic properties and the effects of coadministration with flecainide are unknown, neither disopyramide nor verapamil should be administered concurrently with flecainide unless, in the judgment of the physician, the benefits of this combination outweigh the risks. There has been too little experience with the coadministration of flecainide with nifedipine or diltiazem to recommend concomitant use.

Carcinogenesis, Mutagenesis, Impairment of Fertility

Long-term studies with flecainide in rats and mice at doses up to 60 mg/kg/day have not revealed any compound-related carcinogenic effects. Mutagenicity studies (Ames test, mouse lymphoma and in vivocytogenetics) did not reveal any mutagenic effects. A rat reproduction study at doses up to 50 mg/kg/day (seven times the usual human dose) did not reveal any adverse effect on male or female fertility.

Pregnancy

Pregnancy Category C

Flecainide has been shown to have teratogenic effects (club paws, sternebrae and vertebrae abnormalities, pale hearts with contracted ventricular septum) and an embryotoxic effect (increased resorptions) in one breed of rabbit (New Zealand White) when given doses of 30 and 35 mg/kg/day, but not in another breed of rabbit (Dutch Belted) when given doses up to 30 mg/kg/day. No teratogenic effects were observed in rats and mice given doses up to 50 and 80 mg/kg/day, respectively; however, delayed sternebral and vertebral ossification was observed at the high dose in rats. Because there are no adequate and well-controlled studies in pregnant women, flecainide should be used during pregnancy only if the potential benefit justifies the potential risk to the fetus.

Labor and Delivery

It is not known whether the use of flecainide during labor or delivery has immediate or delayed adverse effects on the mother or fetus, affects the duration of labor or delivery, or increases the possibility of forceps delivery or other obstetrical intervention.

Nursing Mothers

Results from a multiple dose study conducted in mothers soon after delivery indicates that flecainide is excreted in human breast milk in concentrations as high as 4 times (with average levels about 2.5 times) corresponding plasma levels; assuming a maternal plasma level at the top of the therapeutic range (1 mcg/mL), the calculated daily dose to a nursing infant (assuming about 700 mL breast milk over 24 hours) would be less than 3 mg.

Pediatric Use

The safety and efficacy of flecainide in the fetus, infant, or child have not been established in double-blind, randomized, placebo-controlled trials (see CLINICAL PHARMACOLOGY, WARNINGS, and DOSAGE AND ADMINISTRATION).

Hepatic Impairment

Since flecainide elimination from plasma can be markedly slower in patients with significant hepatic impairment, flecainide should not be used in such patients unless the potential benefits clearly outweigh the risks. If used, frequent and early plasma level monitoring is required to guide dosage (see Plasma Level Monitoring); dosage increases should be made very cautiously when plasma levels have plateaued (after more than four days).

ADVERSE REACTIONS

In post-myocardial infarction patients with asymptomatic PVCs and non-sustained ventricular tachycardia, flecainide therapy was found to be associated with a 5.1% rate of death and non-fatal cardiac arrest, compared with a 2.3% rate in a matched placebo group. (See WARNINGS.)

Adverse effects reported for flecainide, described in detail in the WARNINGSsection, were new or worsened arrhythmias which occurred in 1% of 108 patients with PSVT and in 7% of 117 patients with PAF; and new or exacerbated ventricular arrhythmias which occurred in 7% of 1330 patients with PVCs, non-sustained or sustained VT. In patients treated with flecainide for sustained VT, 80% (51/64) of proarrhythmic events occurred within 14 days of the onset of therapy. 198 patients with sustained VT experienced a 13% incidence of new or exacerbated ventricular arrhythmias when dosage was initiated at 200 mg/day with slow upward titration, and did not exceed 300 mg/day in most patients. In some patients, flecainide treatment has been associated with episodes of unresuscitatable VT or ventricular fibrillation (cardiac arrest). (See WARNINGS.) New or worsened CHF occurred in 6.3% of 1046 patients with PVCs, non-sustained or sustainedVT. Of 297 patients with sustainedVT, 9.1% experienced new or worsened CHF. New or worsened CHF was reported in 0.4% of 225 patients with supraventricular arrhythmias. There have also been instances of second- (0.5%) or third-degree (0.4%) AV block. Patients have developed sinus bradycardia, sinus pause, or sinus arrest, about 1.2% altogether (see WARNINGS). The frequency of most of these serious adverse events probably increases with higher trough plasma levels, especially when these trough levels exceed 1 mcg/mL.

There have been rare reports of isolated elevations of serum alkaline phosphatase and isolated elevations of serum transaminase levels. These elevations have been asymptomatic and no cause and effect relationship with flecainide has been established. In foreign postmarketing surveillance studies, there have been rare reports of hepatic dysfunction including reports of cholestasis and hepatic failure, and extremely rare reports of blood dyscrasias. Although no cause and effect relationship has been established, it is advisable to discontinue flecainide in patients who develop unexplained jaundice or signs of hepatic dysfunction or blood dyscrasias in order to eliminate flecainide as the possible causative agent.

Incidence figures for other adverse effects in patients with ventricular arrhythmias are based on a multicenter efficacy study, utilizing starting doses of 200 mg/day with gradual upward titration to 400 mg/day. Patients were treated for an average of 4.7 months, with some receiving up to 22 months of therapy. In this trial, 5.4% of patients discontinued due to non-cardiac adverse effects.

Table 1: Most Common Non-Cardiac Effects in Ventricular Arrhythmia Patients Treated with Flecainide in the Multicenter Study
Adverse Effect | Incidence All 429 Patients at Any Dose | Incidence by Dose During Upward Titration
Adverse Effect | Incidence All 429 Patients at Any Dose | 200 mg/Day (N=426) | 300 mg/Day (N=293) | 400 mg/Day (N=100)
Dizziness [Dizziness includes reports of dizziness, lightheadedness, faintness, unsteadiness, near syncope, etc.] | 18.9% | 11.0% | 10.6% | 13.0%
Visual Disturbances [Visual disturbance includes reports of blurred vision, difficulty in focusing, spots before eyes, etc.] | 15.9% | 5.4% | 12.3% | 18.0%
Dyspnea | 10.3% | 5.2% | 7.5% | 4.0%
Headache | 9.6% | 4.5% | 6.1% | 9.0%
Nausea | 8.9% | 4.9% | 4.8% | 6.0%
Fatigue | 7.7% | 4.5% | 4.4% | 3.0%
Palpitation | 6.1% | 3.5% | 2.4% | 7.0%
Chest Pain | 5.4% | 3.1% | 3.8% | 1.0%
Asthenia | 4.9% | 2.6% | 2.0% | 4.0%
Tremor | 4.7% | 2.4% | 3.4% | 2.0%
Constipation | 4.4% | 2.8% | 2.1% | 1.0%
Edema | 3.5% | 1.9% | 1.4% | 2.0%
Abdominal Pain | 3.3% | 1.9% | 2.4% | 1.0%

The following additional adverse experiences, possibly related to flecainide therapy and occurring in 1% to less than 3% of patients, have been reported in acute and chronic studies: Body as a Whole:malaise, fever; Cardiovascular:tachycardia, sinus pause or arrest; Gastrointestinal:vomiting, diarrhea, dyspepsia, anorexia; Skin:rash; Visual:diplopia; Nervous System:hypoesthesia, paresthesia, paresis, ataxia, flushing, increased sweating, vertigo, syncope, somnolence, tinnitus; Psychiatric:anxiety, insomnia, depression.

The following additional adverse experiences, possibly related to flecainide, have been reported in less than 1% of patients: Body as a Whole:swollen lips, tongue and mouth; arthralgia, bronchospasm, myalgia; Cardiovascular:angina pectoris, second-degree and third-degree AV block, bradycardia, hypertension, hypotension; Gastrointestinal:flatulence; Urinary System:polyuria, urinary retention; Hematologic:leukopenia, granulocytopenia, thrombocytopenia; Skin:urticaria, exfoliative dermatitis, pruritus, alopecia; Visual:eye pain or irritation, photophobia, nystagmus; Nervous System:twitching, weakness, change in taste, dry mouth, convulsions, impotence, speech disorder, stupor, neuropathy; Respiratory:pneumonitis/pulmonary infiltration possibly due to chronic flecainide treatment; Psychiatric:amnesia, confusion, decreased libido, depersonalization, euphoria, morbid dreams, apathy.

For patients with supraventricular arrhythmias, the most commonly reported noncardiac adverse experiences remain consistent with those known for patients treated with flecainide for ventricular arrhythmias. Dizziness is possibly more frequent in PAF patients.

To report SUSPECTED ADVERSE REACTIONS, contact Beximco Pharmaceuticals USA Inc. at 877-372-6093 or FDA at 1-800-FDA-1088 or www.fda.gov/medwatch

OVERDOSAGE

No specific antidote has been identified for the treatment of flecainide overdosage. Overdoses ranging up to 8000 mg have been survived, with peak plasma flecainide concentrations as high as 5.3 mcg/mL. Untoward effects in these cases included nausea and vomiting, convulsions, hypotension, bradycardia, syncope, extreme widening of the QRS complex, widening of the QT interval, widening of the PR interval, ventricular tachycardia, AV nodal block, asystole, bundle branch block, cardiac failure, and cardiac arrest. The spectrum of events observed in fatal cases was much the same as that seen in the non-fatal cases. Death has resulted following ingestion of as little as 1000 mg; concomitant overdose of other drugs and/or alcohol in many instances undoubtedly contributed to the fatal outcome. Treatment of overdosage should be supportive and may include the following: removal of unabsorbed drug from the gastrointestinal tract, administration of inotropic agents or cardiac stimulants such as dopamine, dobutamine or isoproterenol; mechanically assisted respiration; circulatory assists such as intra-aortic balloon pumping; and transvenous pacing in the event of conduction block. Because of the long plasma half-life of flecainide (12 to 27 hours in patients receiving usual doses), and the possibility of markedly non-linear elimination kinetics at very high doses, these supportive treatments may need to be continued for extended periods of time.

Hemodialysis is not an effective means of removing flecainide from the body. Since flecainide elimination is much slower when urine is very alkaline (pH 8 or higher), theoretically, acidification of urine to promote drug excretion may be beneficial in overdose cases with very alkaline urine. There is no evidence that acidification from normal urinary pH increases excretion.

DOSAGE AND ADMINISTRATION

For patients with sustained VT, no matter what their cardiac status, flecainide, like other antiarrhythmics, should be initiated in-hospital with rhythm monitoring.

Flecainide has a long half-life (12 to 27 hours in patients). Steady-state plasma levels, in patients with normal renal and hepatic function, may not be achieved until the patient has received 3 to 5 days of therapy at a given dose. Therefore, increases in dosage should be made no more frequently than once every four days, since during the first 2 to 3 days of therapy the optimal effect of a given dose may not be achieved.

For patients with PSVT and patients with PAF the recommended starting dose is 50 mg every 12 hours. Flecainide doses may be increased in increments of 50 mg bid every four days until efficacy is achieved. For PAF patients, a substantial increase in efficacy without a substantial increase in discontinuations for adverse experiences may be achieved by increasing the flecainide dose from 50 mg to 100 mg bid. The maximum recommended dose for patients with paroxysmal supraventricular arrhythmias is 300 mg/day.

For sustained VT the recommended starting dose is 100 mg every 12 hours. This dose may be increased in increments of 50 mg bid every four days until efficacy is achieved. Most patients with sustained VT do not require more than 150 mg every 12 hours (300 mg/day), and the maximum dose recommended is 400 mg/day.

In patients with sustained VT, use of higher initial doses and more rapid dosage adjustments have resulted in an increased incidence of proarrhythmic events and CHF, particularly during the first few days of dosing (See WARNINGS). Therefore, a loading dose is not recommended.

Intravenous lidocaine has been used occasionally with flecainide while awaiting the therapeutic effect of flecainide. No adverse drug interactions were apparent. However, no formal studies have been performed to demonstrate the usefulness of this regimen.

An occasional patient not adequately controlled by (or intolerant to) a dose given at 12-hour intervals may be dosed at eight-hour intervals.

Once adequate control of the arrhythmia has been achieved, it may be possible in some patients to reduce the dose as necessary to minimize side effects or effects on conduction. In such patients, efficacy at the lower dose should be evaluated. Flecainide should be used cautiously in patients with a history of CHF or myocardial dysfunction (See WARNINGS).

Any use of flecainide in children should be directly supervised by a cardiologist skilled in the treatment of arrhythmias in children. Because of the evolving nature of information in this area, specialized literature should be consulted. Under six months of age, the initial starting dose of flecainide in children is approximately 50 mg/M2 body surface area daily, divided into two or three equally spaced doses. Over six months of age, the initial starting dose may be increased to 100 mg/M2 per day. The maximum recommended dose is 200 mg/M2 per day. This dose should not be exceeded. In some children on higher doses, despite previously low plasma levels, the level has increased rapidly to far above therapeutic values while taking the same dose. Small changes in dose may also lead to disproportionate increases in plasma levels. Plasma trough (less than one hour pre-dose) flecainide levels and electrocardiograms should be obtained at presumed steady state (after at least five doses) either after initiation or change in flecainide dose, whether the dose was increased for lack of effectiveness, or increased growth of the patient. For the first year on therapy, whenever the patient is seen for reasons of clinical follow-up, it is suggested that a 12-lead electrocardiogram and plasma trough flecainide level are obtained. The usual therapeutic level of flecainide in children is 200 to 500 ng/mL. In some cases, levels as high as 800 ng/mL may be required for control.

In patients with severe renal impairment (creatinine clearance of 35 mL/min/1.73 square meters or less), the initial dosage should be 100 mg once daily (or 50 mg bid); when used in such patients, frequent plasma level monitoring is required to guide dosage adjustments (See PLASMA LEVEL MONITORING). In patients with less severe renal disease, the initial dosage should be 100 mg every 12 hours; plasma level monitoring may also be useful in these patients during dosage adjustment. In both groups of patients, dosage increases should be made very cautiously when plasma levels have plateaued (after more than four days), observing the patient closely for signs of adverse cardiac effects or other toxicity. It should be borne in mind that in these patients it may take longer than four days before a new steady-state plasma level is reached following a dosage change.

Based on theoretical considerations, rather than experimental data, the following suggestion is made: when transferring patients from another antiarrhythmic drug to flecainide allow at least two to four plasma half-lives to elapse for the drug being discontinued before starting flecainide at the usual dosage. In patients where withdrawal of a previous antiarrhythmic agent is likely to produce life-threatening arrhythmias, the physician should consider hospitalizing the patient.

When flecainide is given in the presence of amiodarone, reduce the usual flecainide dose by 50% and monitor the patient closely for adverse effects.

Plasma level monitoring is strongly recommended to guide dosage with such combination therapy (See below).

Plasma Level Monitoring

The large majority of patients successfully treated with flecainide were found to have trough plasma levels between 0.2 and 1 mcg/mL. The probability of adverse experiences, especially cardiac, may increase with higher trough plasma levels, especially when these exceed 1 mcg/mL. Periodic monitoring of trough plasma levels may be useful in patient management. Plasma level monitoring is required in patients with severe renal failure or severe hepatic disease, since elimination of flecainide from plasma may be markedly slower. Monitoring of plasma levels is strongly recommended in patients on concurrent amiodarone therapy and may also be helpful in patients with CHF and in patients with moderate renal disease.

HOW SUPPLIED

Flecainide acetate tablets, USP are supplied as white to off white, round shaped tablets for the 100 mg strength.

The 100 mg tablets are scored on one side and debossed with "BPL026" on the other side.

Bottle of 60 NDC 72789-383-60

Bottle of 100 NDC 72789-383-01

Bottle of 180 NDC 72789-383-93

STORAGE

Store at 20°C to 25°C (68°F to 77°F). [See USP Controlled Room Temperature.] Store in a tight, light-resistant container.

Rev. 11/2025